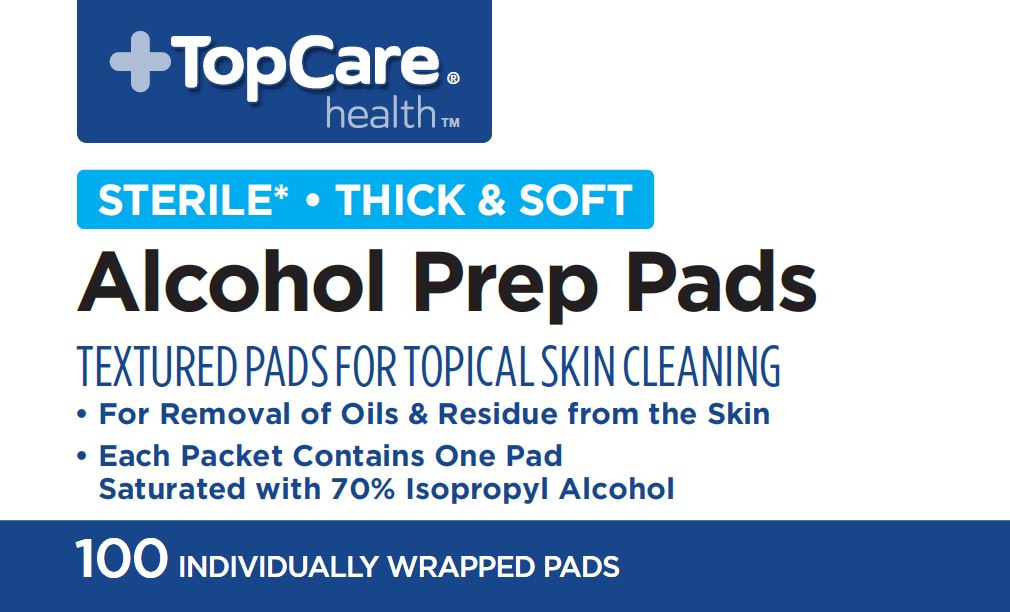 DRUG LABEL: Alcohol Prep
NDC: 76162-809 | Form: SWAB
Manufacturer: Topco Associates
Category: otc | Type: HUMAN OTC DRUG LABEL
Date: 20231227

ACTIVE INGREDIENTS: ISOPROPYL ALCOHOL 70 mL/100 mL
INACTIVE INGREDIENTS: WATER

76162-809 Top Care IPA Pads

Active ingredient

Isopropyl Alcohol, 70% v/v

Purpose

Antiseptic

Uses

- First aid to decrease germs in minor cuts, scrapes and burns.

Warnings

- For external use only.
- Flammable. Keep away from fire or flame.

Do not use

- with electrocautery procedures
- longer than 1 week unless directed by a doctor

When using this product

- do not get into eyes
- do not apply over large areas of the body
- in case of deep or puncture wounds, animal bites or serious burns, consult a doctor

Stop use and ask a doctor if

- irritation and redness develop
- condition gets worse or persists for more than 72 hours

Keep out of reach of children.

If accidentally swallowed, get medical help or contact a Poison Control Center right away.

Directions

- Apply to skin as needed
- Discard after single use

Other information

Protect from freezing and avoid excessive heat.

Inactive ingredients

water

Manufacturing Information

Distributed By:

Topco Associates LLC.

Elk Grove Village, IL 60007

©TopCo MDLA0618

Questions? 1-888-423-0139

topcare@topco.com

www.topcarebrand.com

Made in China

RD20LPD